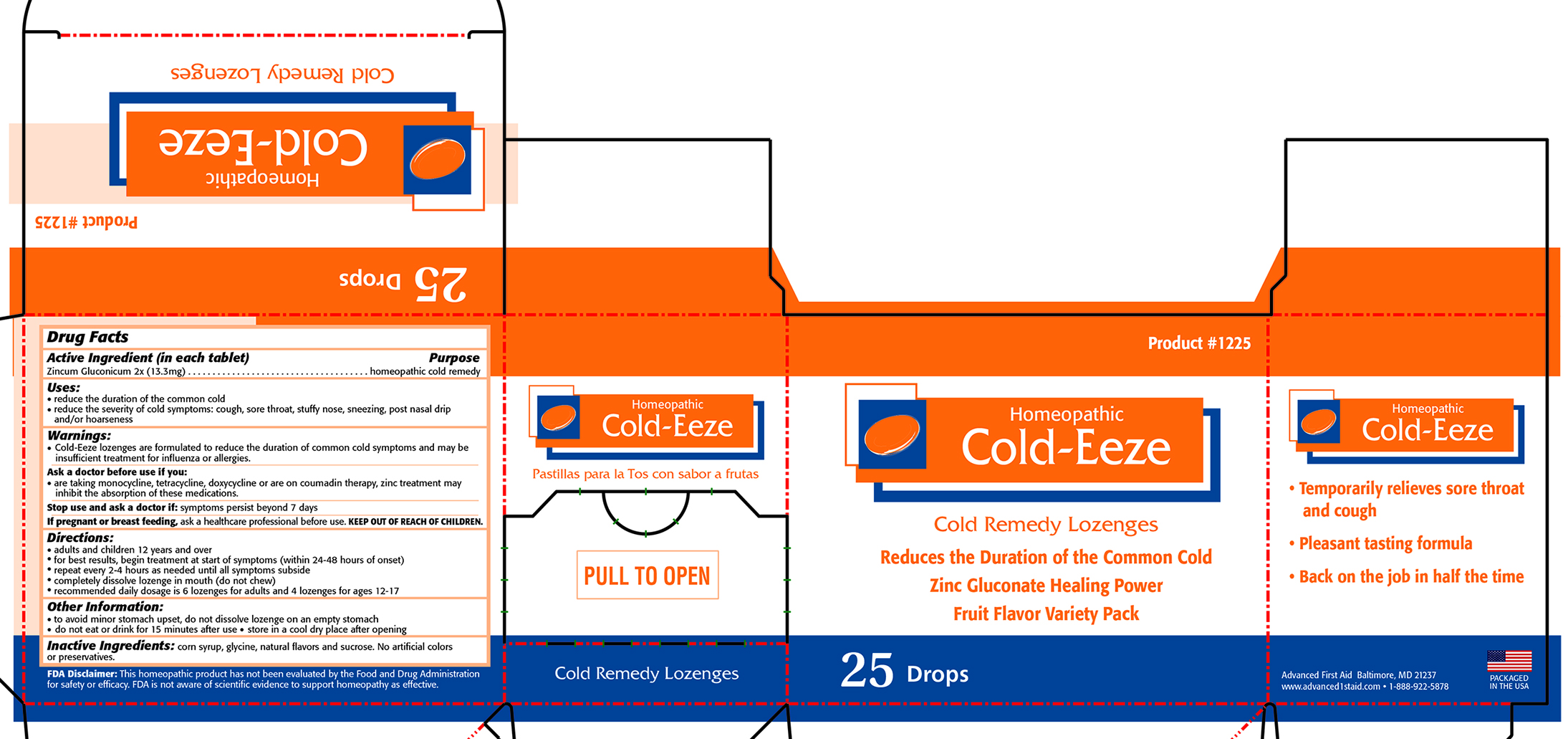 DRUG LABEL: ADVANCED HOMEOPATHIC COLD-EEZE
NDC: 67060-122 | Form: LOZENGE
Manufacturer: ADVANCED FIRST AID, INC.
Category: homeopathic | Type: HUMAN OTC DRUG LABEL
Date: 20190916

ACTIVE INGREDIENTS: ZINC GLUCONATE 2 [hp_X]/1 1
INACTIVE INGREDIENTS: CORN SYRUP; GLYCINE; SUCROSE

Advanced Homeopathic Cold-Eeze

Active Ingredient (in each tablet) - Zincum Gluconicum 2x (13.3mg)

PURPOSE

homeopathic cold remedy

Uses:

- reduce the duration of the common cold
- reduce the severity of cold symptoms: cough, sore throat, stuffy nose, sneezing, post nasal drip and/or hoarseness

Warnings:

- Cold-Eeze lozenges are formulated to reduce the duration of common cold smptoms and may be insufficient treatment for influenza or allergies.

Ask a doctor before use if you:

- are taking monocycline, tetracycline, doxycycline or are on coumadin therapy, zinc treatment may inhibit the absorption of these medications.

Stop use and ask a doctor if:

- symptoms persist beyond 7 days

PREGNANCY OR BREAST FEEDING

If pregnant or breastfeeding, ask a healthcare professional before use.

Directions:

- adults and children 12 years and over
- for best results, begin treatment at start of symptoms (within 24-48 hours of onset)
- repeat ever 2-4 hours as needed until all symptoms subside
- completely dissolve lozenge in mouth (do not chew)
- recommended daily dosage is 6 lozenges for adults and 4 lozenges for ages 12-17

OTHER SAFETY INFORMATION

- to avoid minor stomach upset, do not dissolve lozenge on an empty stomach
- do not eat or drink for 15 minutes after use
- store in a cool dry place after opening

INACTIVE INGREDIENT

Inactive Ingredients: corn syrup, glycine, natural flavors and sucrose. No artificial colors or preservatives.